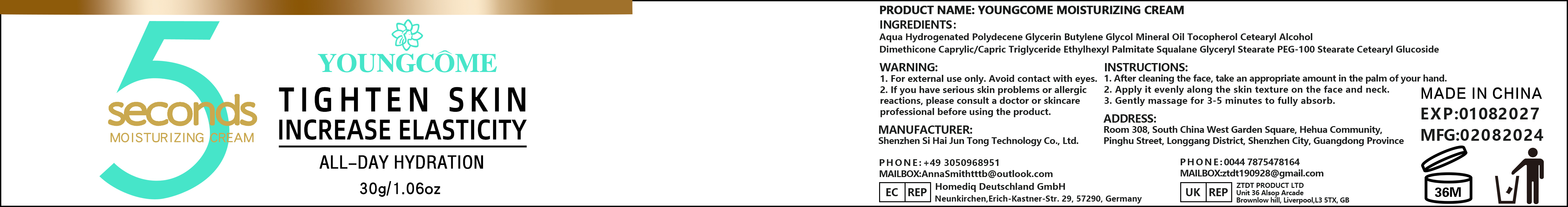 DRUG LABEL: YOUNGCOMEMOISTURIZINGCREAM
NDC: 84350-005 | Form: CREAM
Manufacturer: Shenzhen Sihai Juntong Technology Co., Ltd
Category: otc | Type: HUMAN OTC DRUG LABEL
Date: 20240813

ACTIVE INGREDIENTS: SQUALANE 1 g/100 mg
INACTIVE INGREDIENTS: WATER 1 g/100 mg

ACTIVE INGREDIENT

Tocopherol 5%

INACTIVE INGREDIENT

Water 5%

PURPOSE

Moisturizing

WARNINGS

1. For external use only. Avoid contact with eyes. 2. lf you have serious skin problems or allergic reactions, pleaseconsult a doctor or skincare professional before using the product.

Do not use

if you have allergic reactions, stop to use

WHEN USING

1. After cleaning the face, take an appropriate amount in the palm of your hand.2.Apply it evenly along the skin texture on the face and neck.3.Gently massage for 3-5 minutes to fully absorb.

Keep out of reach of children

INDICATIONS AND USAGE

1. After cleaning the face, take an appropriate amount in the palm of your hand.2.Apply it evenly along the skin texture on the face and neck.3.Gently massage for 3-5 minutes to fully absorb.

Dosage and administration

appropriate amount

PACKAGE LABEL

30g NDC:84350-005-01